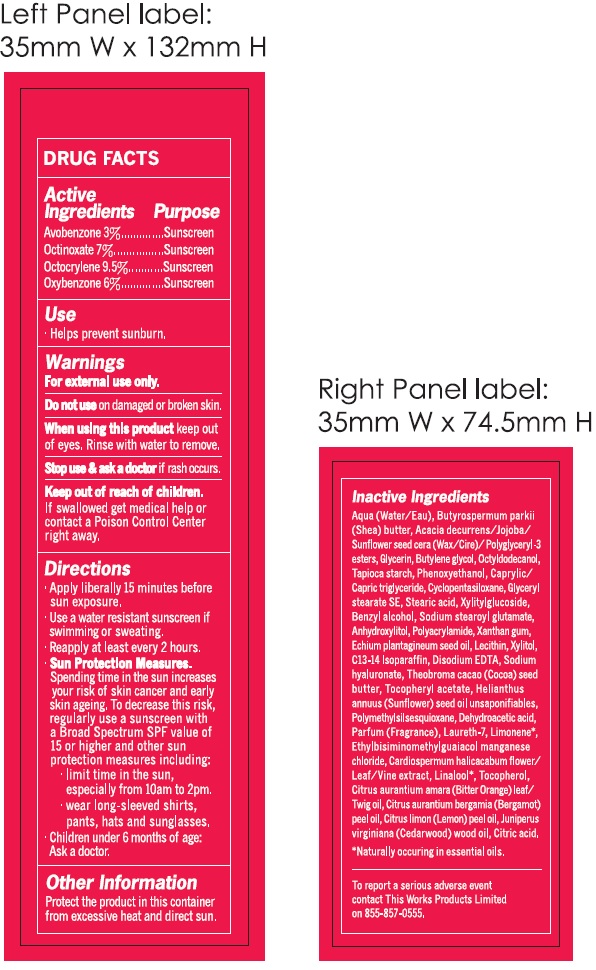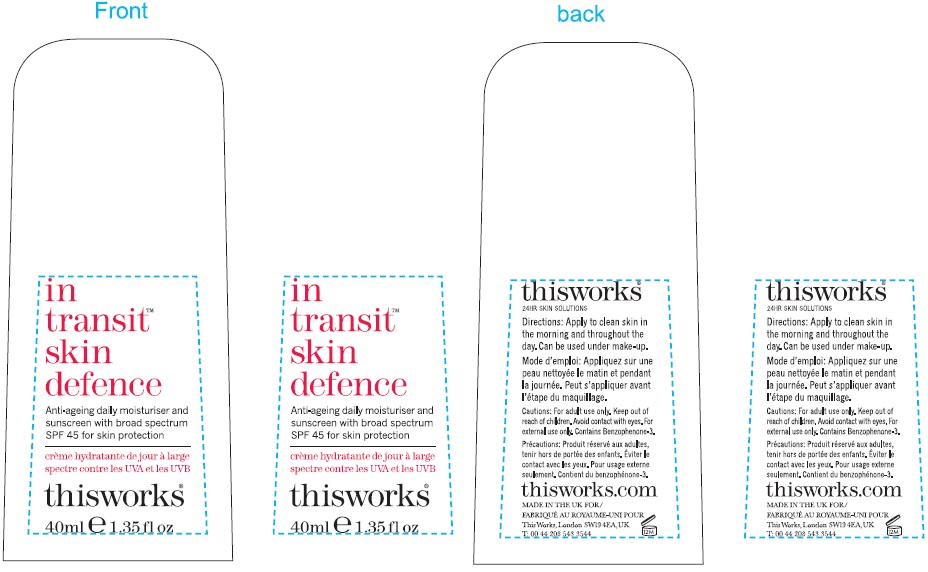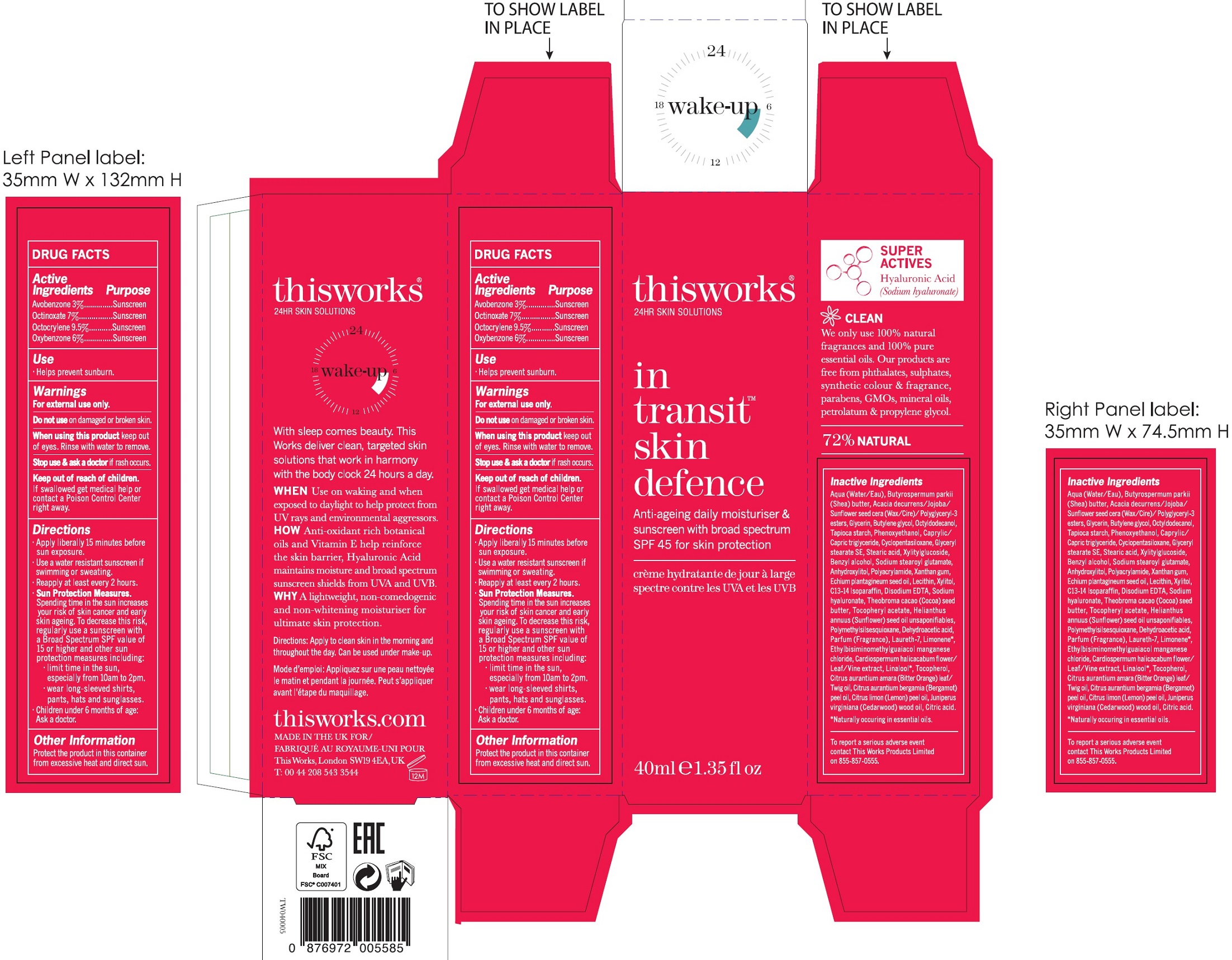 DRUG LABEL: In Transit Skin Defence
NDC: 71278-006 | Form: CREAM
Manufacturer: THIS WORKS PRODUCTS LIMITED
Category: otc | Type: HUMAN OTC DRUG LABEL
Date: 20231114

ACTIVE INGREDIENTS: AVOBENZONE 30 mg/1 mL; OCTINOXATE 70 mg/1 mL; OCTOCRYLENE 95 mg/1 mL; OXYBENZONE 60 mg/1 mL
INACTIVE INGREDIENTS: WATER; SHEA BUTTER; GLYCERIN; BUTYLENE GLYCOL; OCTYLDODECANOL; STARCH, TAPIOCA; PHENOXYETHANOL; MEDIUM-CHAIN TRIGLYCERIDES; CYCLOMETHICONE 5; GLYCERYL STEARATE SE; STEARIC ACID; XYLITYLGLUCOSIDE; BENZYL ALCOHOL; SODIUM STEAROYL GLUTAMATE; ANHYDROXYLITOL; XANTHAN GUM; ECHIUM PLANTAGINEUM SEED OIL; XYLITOL; C13-14 ISOPARAFFIN; EDETATE DISODIUM ANHYDROUS; HYALURONATE SODIUM; COCOA BUTTER; .ALPHA.-TOCOPHEROL ACETATE; HELIANTHUS ANNUUS FLOWERING TOP; POLYMETHYLSILSESQUIOXANE (4.5 MICRONS); DEHYDROACETIC ACID; LAURETH-7; LIMONENE, (+)-; ETHYLBISIMINOMETHYLGUAIACOL MANGANESE CHLORIDE; CARDIOSPERMUM HALICACABUM FLOWERING TOP; LINALOOL, (+/-)-; TOCOPHEROL; CITRUS AURANTIUM LEAFY TWIG OIL; BERGAMOT OIL; LEMON OIL; JUNIPERUS VIRGINIANA OIL; CITRIC ACID MONOHYDRATE

In Transit Skin Defence

Active Ingredients

Avobenzone 3%

Octinoxate 7%

Octocrylene 9.5%

Oxybenzone 6%

Purpose

Sunscreen

Use

- Helps prevent sunburn.

Warnings

For external use only.

Do not use

on damaged or broken skin.

When using this product

keep out of eyes. Rinse with water to remove.

Stop use and ask a doctor

if rash occurs.

Keep out of reach of children.

If swallowed get medical help or contact a Poison Control Center right away.

Directions

- Apply liberally 15 minutes before sun exposure.
- Use a water resistant sunscreen if swimming or sweating.
- Reapply at least every 2 hours.
- Spending time in the sun increases your risk of skin cancer and early skin ageing. To decrease this risk, regularly use a sunscreen with a Broad Spectrum SPF value of 15 or higher and other sun protection measures including: Sun Protection Measures.
- limit time in the sun, especially from 10am to2pm.
- wear long-sleeved shirts, pants, hats and sunglasses.
- Children under 6 months of age: Ask a doctor.

Other Information

Protect the product in this container from excessive heat and direct sun.

Inactive Ingredients

Aqua (Water/Eau), Butyrospermum parkii (Shea) butter, Acacia decurrens/Jojoba/Sunflower seed cera (Wax/Cire)/Polyglyceryl-3 esters, Glycerin, Butylene glycol, Octyldodecanol, Tapioca starch, Phenoxyethanol, Caprylic/Capric Triglyceride, Cyclopentasiloxane, Glyceryl stearate SE, Stearic acid, Xylitylglucoside, Benzyl alcohol, Sodium stearoyl glutamate, Anhydroxylitol, Polyacrylamide, Xanthan gum, Echium plantagineum seed oil, Lecithin, Xylitol, C13-14 Isoparaffin, Disodium EDTA, Sodium hyaluronate, Theobroma cacao (Cocoa) seed butter, Tocopheryl acetate, Helianthus annuus (Sunflower) seed oil unsaponifiables, Polymethylsilsesquioxane, Dehydroacetic acid, Parfum (Fragrance), Laureth-7, Limonene, Ethylbisiminomethylguaiacol manganese chloride, Cardiospermum halicacabum flower/Leaf/Vine extract, Linalool, Tocopherol, Citrus aurantium amara (Bitter Orange) leaf/Twig oil, Citrus aurantium bergamia (Bergamot) peel oil, Citrus limon (Lemon) peel oil, juniperus virginiana (Cedarwood) wood oil, Citric acid. *Naturally occuring i essential oils.

QUESTIONS

To report serious adverse even contact This Works Products Limited on 855-877-0555.